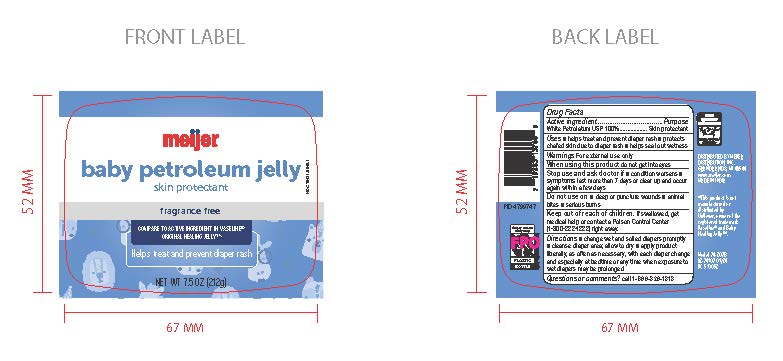 DRUG LABEL: Meijer Baby Petroleum Jelly Skin Protectant Frag Free
NDC: 79481-0046 | Form: GEL
Manufacturer: Meijer Distribution
Category: otc | Type: HUMAN OTC DRUG LABEL
Date: 20240826

ACTIVE INGREDIENTS: PETROLATUM 100 g/100 g
INACTIVE INGREDIENTS: WATER

Meijer Baby Petroleum Jelly Skin Protectant Frag Free

Active Ingredients

White Petrolatum USP 100%

Purpose

Skin Protectant

Uses

Uses ■ helps treat and prevent diaper rash ■ protects chafed skin due to diaper rash ■ helps seal
out wetness Warnings For external use only

Warnings

For external use only

When using this product

do not get into eyes

Stop use and ask doctor if ■ condition worsens ■ symptoms last more than 7 days or clear up and
occur again within a few days

Do not use on ■ deep or puncture wounds ■ animal bites ■ serious burns

Keep out of reach of children. If swallowed get medical help or contact a Poison Control Center (1-800-222-1222) right away.

Directions

■ change wet and soiled diapers promptly
■ cleanse diaper area; allow to dry

■ apply product liberally, as often as necessary, with each diaper change and especially at bedtime or any time when exposure to
wet diapers may be prolonged

Questions or comments? call 1-866-326-1313

Inactive Ingredient

Water